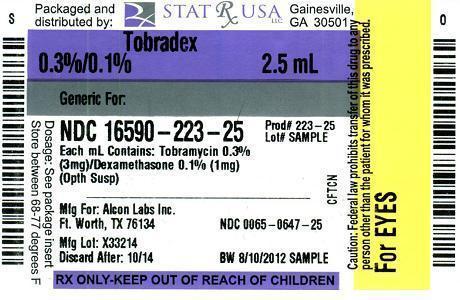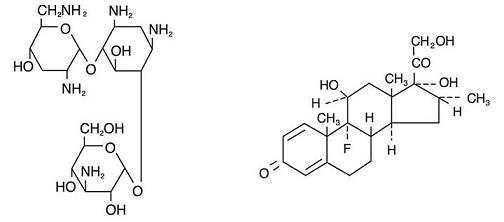 DRUG LABEL: TOBRADEX
NDC: 16590-223 | Form: SUSPENSION
Manufacturer: STAT Rx USA LLC
Category: prescription | Type: HUMAN PRESCRIPTION DRUG LABEL
Date: 20120830

ACTIVE INGREDIENTS: TOBRAMYCIN 3 mg/1 mL; DEXAMETHASONE 1 mg/1 mL
INACTIVE INGREDIENTS: BENZALKONIUM CHLORIDE; TYLOXAPOL; EDETATE DISODIUM; SODIUM CHLORIDE; HYDROXYETHYL CELLULOSE (2000 CPS AT 1%); SODIUM SULFATE; SULFURIC ACID; SODIUM HYDROXIDE; WATER

TobraDex®
(tobramycin and dexamethasone ophthalmic suspension) Sterile

DESCRIPTION

TOBRADEX® (tobramycin and dexamethasone ophthalmic suspension) is a sterile, multiple dose antibiotic and steroid combination for topical ophthalmic use.

The chemical structures for tobramycin and dexamethasone are presented below:

Tobramycin

Empirical Formula: C18H37N5O9

Chemical Name: O-3-Amino-3-deoxy-α-D-glucopyranosyl-(1→4)-O-[2,6-diamino-2,3,6-trideoxy-α-D-ribo-hexopyranosyl-(1→6)]-2-deoxy-L-streptamine

Dexamethasone

Empirical Formula: C22H29FO5

Chemical Name: 9-Fluoro-11β,17,21-trihydroxy-16α-methylpregna-1,4-diene-3,20-dione

Each mL of TOBRADEX® (tobramycin and dexamethasone ophthalmic suspension) contains: Actives: tobramycin 0.3% (3 mg) and dexamethasone 0.1% (1 mg). Preservative: benzalkonium chloride 0.01%. Inactives: tyloxapol, edetate disodium, sodium chloride, hydroxyethyl cellulose, sodium sulfate, sulfuric acid and/or sodium hydroxide (to adjust pH) and purified water.

CLINICAL PHARMACOLOGY

Corticoids suppress the inflammatory response to a variety of agents and they probably delay or slow healing. Since corticoids may inhibit the body's defense mechanism against infection, a concomitant antimicrobial drug may be used when this inhibition is considered to be clinically significant. Dexamethasone is a potent corticoid.

The antibiotic component in the combination (tobramycin) is included to provide action against susceptible organisms. In vitro studies have demonstrated that tobramycin is active against susceptible strains of the following microorganisms:

Staphylococci, including S. aureus and S. epidermidis (coagulase-positive and coagulase-negative), including penicillin-resistant strains.

Streptococci, including some of the Group A-beta-hemolytic species, some nonhemolytic species, and some Streptococcus pneumoniae.

Pseudomonas aeruginosa, Escherichia coli, Klebsiella pneumoniae, Enterobacter aerogenes, Proteus mirabilis, Morganella morganii, most Proteus vulgaris strains, Haemophilus influenzae and H. aegyptius, Moraxella lacunata, Acinetobacter calcoaceticus and some Neisseria species.

Bacterial susceptibility studies demonstrate that in some cases microorganisms resistant to gentamicin remain susceptible to tobramycin.

No data are available on the extent of systemic absorption from TOBRADEX® (tobramycin and dexamethasone ophthalmic suspension); however, it is known that some systemic absorption can occur with ocularly applied drugs. If the maximum dose of TOBRADEX® (tobramycin and dexamethasone ophthalmic suspension) is given for the first 48 hours (two drops in each eye every 2 hours) and complete systemic absorption occurs, which is highly unlikely, the daily dose of dexamethasone would be 2.4 mg. The usual physiologic replacement dose is 0.75 mg daily. If TOBRADEX® (tobramycin and dexamethasone ophthalmic suspension) is given after the first 48 hours as two drops in each eye every 4 hours, the administered dose of dexamethasone would be 1.2 mg daily.

INDICATIONS AND USAGE

TOBRADEX® (tobramycin and dexamethasone ophthalmic suspension) is indicated for steroid-responsive inflammatory ocular conditions for which a corticosteroid is indicated and where superficial bacterial ocular infection or a risk of bacterial ocular infection exists.

Ocular steroids are indicated in inflammatory conditions of the palpebral and bulbar conjunctiva, cornea and anterior segment of the globe where the inherent risk of steroid use in certain infective conjunctivitides is accepted to obtain a diminution in edema and inflammation. They are also indicated in chronic anterior uveitis and corneal injury from chemical, radiation or thermal burns, or penetration of foreign bodies.

The use of a combination drug with an anti-infective component is indicated where the risk of superficial ocular infection is high or where there is an expectation that potentially dangerous numbers of bacteria will be present in the eye.

The particular anti-infective drug in this product is active against the following common bacterial eye pathogens:

Staphylococci, including S. aureus and S. epidermidis (coagulase-positive and coagulase-negative), including penicillin-resistant strains.

Streptococci, including some of the Group A-beta-hemolytic species, some nonhemolytic species, and some Streptococcus pneumoniae.

Pseudomonas aeruginosa, Escherichia coli, Klebsiella pneumoniae, Enterobacter aerogenes, Proteus mirabilis, Morganella morganii, most Proteus vulgaris strains, Haemophilus influenzae and H. aegyptius, Moraxella lacunata, Acinetobacter calcoaceticus and some Neisseria species.

CONTRAINDICATIONS

Epithelial herpes simplex keratitis (dendritic keratitis), vaccinia, varicella, and many other viral diseases of the cornea and conjunctiva. Mycobacterial infection of the eye. Fungal diseases of ocular structures. Hypersensitivity to a component of the medication.

WARNINGS

FOR TOPICAL OPHTHALMIC USE ONLY. NOT FOR INJECTION INTO THE EYE. Sensitivity to topically applied aminoglycosides may occur in some patients. If a sensitivity reaction does occur, discontinue use.

Prolonged use of steroids may result in glaucoma, with damage to the optic nerve, defects in visual acuity and fields of vision, and posterior subcapsular cataract formation. Intraocular pressure should be routinely monitored even though it may be difficult in pediatric patients and uncooperative patients. Prolonged use may suppress the host response and thus increase the hazard of secondary ocular infections. In those diseases causing thinning of the cornea or sclera, perforations have been known to occur with the use of topical steroids. In acute purulent conditions of the eye, steroids may mask infection or enhance existing infection.

PRECAUTIONS

General

The possibility of fungal infections of the cornea should be considered after long-term steroid dosing. As with other antibiotic preparations, prolonged use may result in overgrowth of nonsusceptible organisms, including fungi. If superinfection occurs, appropriate therapy should be initiated. When multiple prescriptions are required, or whenever clinical judgement dictates, the patient should be examined with the aid of magnification, such as slit lamp biomicroscopy and, where appropriate, fluorescein staining.

Cross-sensitivity to other aminoglycoside antibiotics may occur; if hypersensitivity develops with this product, discontinue use and institute appropriate therapy.

Information for Patients

Do not touch dropper tip to any surface, as this may contaminate the contents. Contact lenses should not be worn during the use of this product.

Carcinogenesis, Mutagenesis, Impairment of Fertility

No studies have been conducted to evaluate the carcinogenic or mutagenic potential. No impairment of fertility was noted in studies of subcutaneous tobramycin in rats at doses of 50 and 100 mg/kg/day.

Pregnancy Category C

Corticosteroids have been found to be teratogenic in animal studies. Ocular administration of 0.1% dexamethasone resulted in 15.6% and 32.3% incidence of fetal anomalies in two groups of pregnant rabbits. Fetal growth retardation and increased mortality rates have been observed in rats with chronic dexamethasone therapy. Reproduction studies have been performed in rats and rabbits with tobramycin at doses up to 100 mg/kg/day parenterally and have revealed no evidence of impaired fertility or harm to the fetus. There are no adequate and well controlled studies in pregnant women. TOBRADEX® (tobramycin and dexamethasone ophthalmic suspension) should be used during pregnancy only if the potential benefit justifies the potential risk to the fetus.

Nursing Mothers

Systemically administered corticosteroids appear in human milk and could suppress growth, interfere with endogenous corticosteroid production, or cause other untoward effects. It is not known whether topical administration of corticosteroids could result in sufficient systemic absorption to produce detectable quantities in human milk. Because many drugs are excreted in human milk, caution should be exercised when TOBRADEX® (tobramycin and dexamethasone ophthalmic suspension) is administered to a nursing woman.

Pediatric Use

Safety and effectiveness in pediatric patients below the age of 2 years have not been established.

Geriatric Use

No overall differences in safety or effectiveness have been observed between elderly and younger patients.

ADVERSE REACTIONS

Adverse reactions have occurred with steroid/anti-infective combination drugs which can be attributed to the steroid component, the anti-infective component, or the combination. Exact incidence figures are not available. The most frequent adverse reactions to topical ocular tobramycin [TOBREX® (tobramycin ophthalmic solution)] are hypersensitivity and localized ocular toxicity, including lid itching and swelling, and conjunctival erythema. These reactions occur in less than 4% of patients. Similar reactions may occur with the topical use of other aminoglycoside antibiotics. Other adverse reactions have not been reported; however, if topical ocular tobramycin is administered concomitantly with systemic aminoglycoside antibiotics, care should be taken to monitor the total serum concentration. The reactions due to the steroid component are: elevation of intraocular pressure (IOP) with possible development of glaucoma, and infrequent optic nerve damage; posterior subcapsular cataract formation; and delayed wound healing.

Secondary Infection. The development of secondary infection has occurred after use of combinations containing steroids and antimicrobials. Fungal infections of the cornea are particularly prone to develop coincidentally with long-term applications of steroids. The possibility of fungal invasion must be considered in any persistent corneal ulceration where steroid treatment has been used. Secondary bacterial ocular infection following suppression of host responses also occurs.

OVERDOSAGE

Clinically apparent signs and symptoms of an overdosage of TOBRADEX® (tobramycin and dexamethasone ophthalmic suspension) punctate keratitis, erythema, increased lacrimation, edema and lid itching may be similar to adverse reaction effects seen in some patients.

DOSAGE AND ADMINISTRATION

One or two drops instilled into the conjunctival sac(s) every four to six hours. During the initial 24 to 48 hours, the dosage may be increased to one or two drops every two (2) hours. Frequency should be decreased gradually as warranted by improvement in clinical signs. Care should be taken not to discontinue therapy prematurely.

Not more than 20 mL should be prescribed initially and the prescription should not be refilled without further evaluation as outlined in PRECAUTIONS above.

HOW SUPPLIED

Sterile ophthalmic suspension in 2.5 mL - NDC 16590-223-25

STORAGE: Store at 8°-27°C (46°-80°F).

Store suspension upright and shake well before using.

Rx Only

©2002, 2006, 2010 Alcon, Inc.

ALCON LABORATORIES, INC.

Fort Worth, Texas 76134 USA

Printed in USA

Revised: April 2010

9001599-0410

Relabeling by:

STAT Rx USA LLC

Gainesville, GA 30501